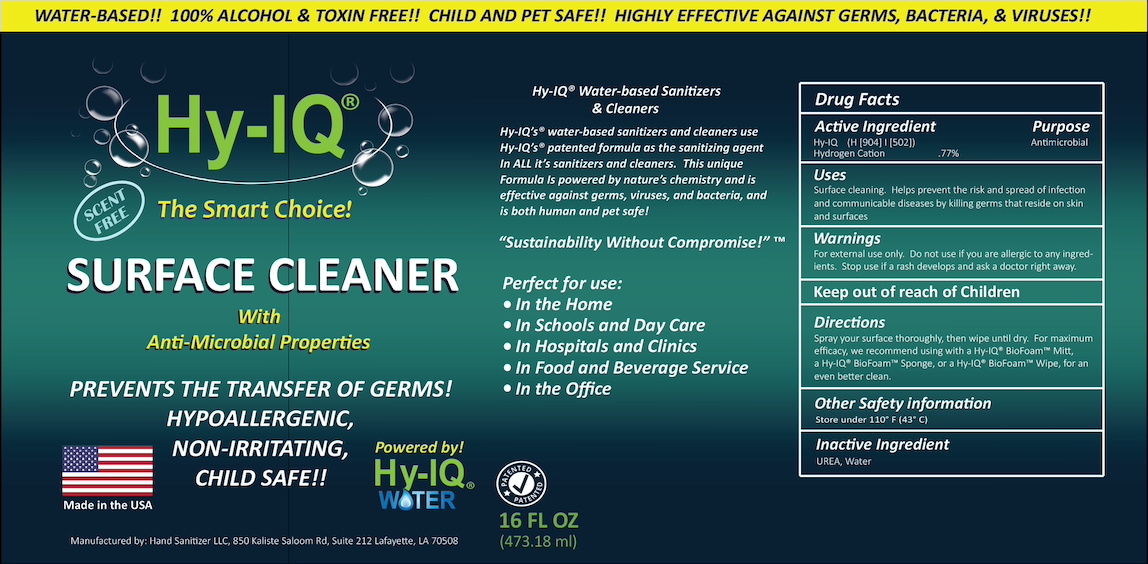 DRUG LABEL: HY-IQ SURFACE CLEANER
NDC: 76701-361 | Form: SPRAY
Manufacturer: HAND SANITIZER LLC
Category: otc | Type: HUMAN OTC DRUG LABEL
Date: 20210623

ACTIVE INGREDIENTS: HYDROGEN CATION 10 mg/1 mL
INACTIVE INGREDIENTS: WATER 940 mg/1 mL; UREA 50 mg/1 mL

ACTIVE INGREDIENT

Hy- IQ Water ([H9O4] | [H5O2])

Hydrogen Cation .77%

PURPOSE

Antiseptic

INDICATIONS AND USAGE

Surface cleaning. Helps prevent the risk and spread of infection and communicable diseases by killing germs that reside on skin and surfaces.

WARNINGS

For external use only. Do not use if you are allergic to any ingredients. Stop use if a rash develops and ask a doctor right away.

Keep Out of Reach of Children

DOSAGE AND ADMINISTRATION

Spray your surface throroughly, then wipe until dry. For maximum efficacy, we recommend using with a Hy-IQ® BioFoam™ Mitt, a Hy-IQ® Biofoam™ Sponge, or a Hy-IQ® BioFoam™ Wipe, for an even better clean.

OTHER SAFETY INFORMATION

Store under 110°F (43°C)

INACTIVE INGREDIENT

WATER, UREA

PACKAGE LABEL

Hy-IQ Surface Cleaner